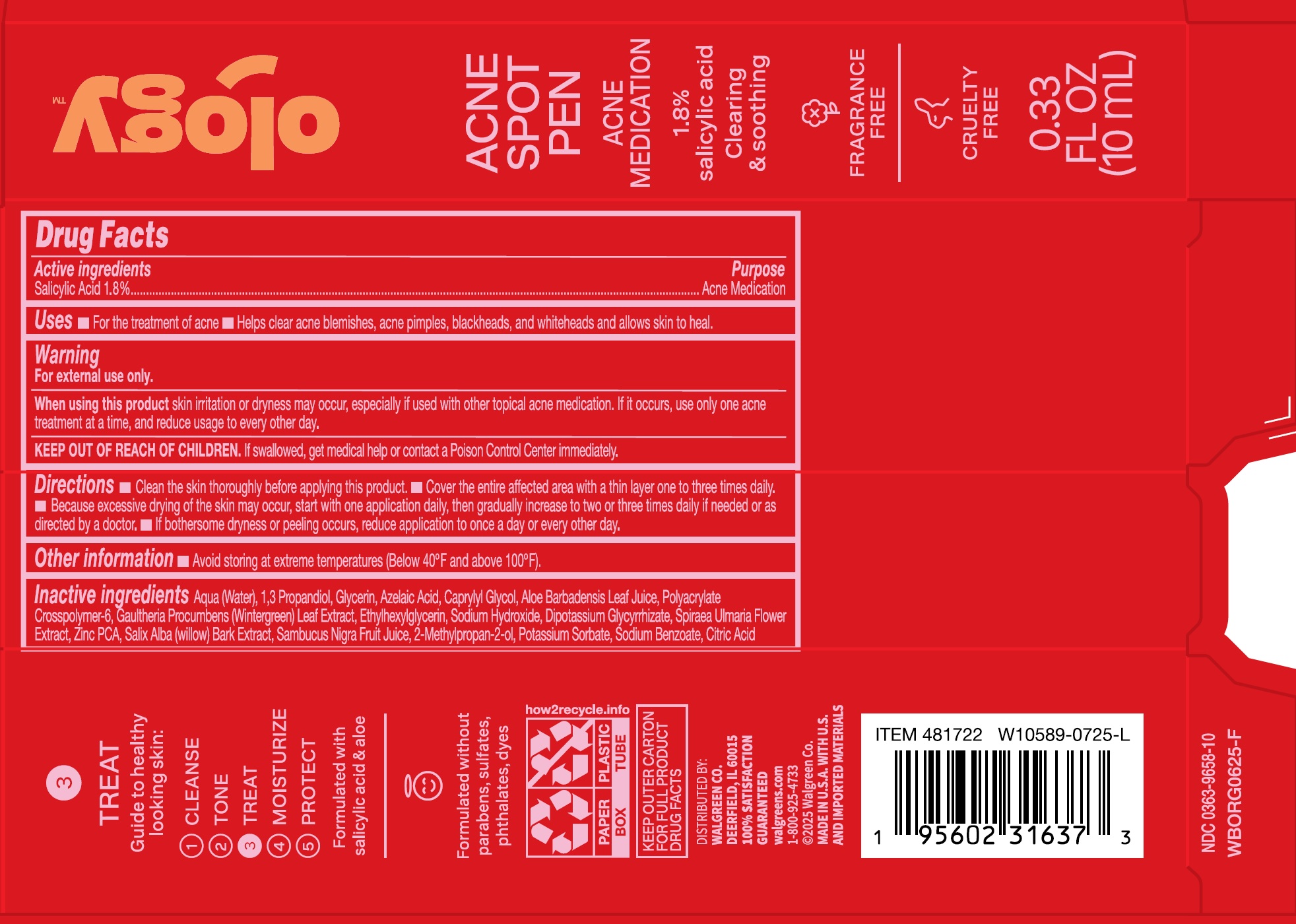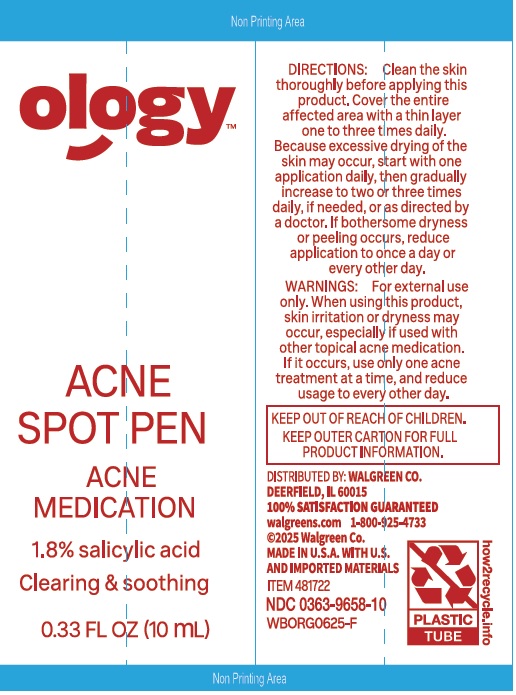 DRUG LABEL: Ology Acne Spot
NDC: 0363-9658 | Form: GEL
Manufacturer: Walgreens Co.
Category: otc | Type: HUMAN OTC DRUG LABEL
Date: 20250905

ACTIVE INGREDIENTS: SALICYLIC ACID 18 mg/1 mL
INACTIVE INGREDIENTS: WATER; PROPANEDIOL; GLYCERIN; AZELAIC ACID; CAPRYLYL GLYCOL; ALOE VERA LEAF JUICE; AMMONIUM ACRYLOYLDIMETHYLTAURATE, DIMETHYLACRYLAMIDE, LAURYL METHACRYLATE AND LAURETH-4 METHACRYLATE COPOLYMER, TRIMETHYLOLPROPANE TRIACRYLATE CROSSLINKED (45000 MPA.S); GAULTHERIA PROCUMBENS LEAF; ETHYLHEXYLGLYCERIN; SODIUM HYDROXIDE; DIPOTASSIUM GLYCYRRHIZATE; FILIPENDULA ULMARIA FLOWER; ZINC PIDOLATE; SALIX ALBA BARK; EUROPEAN ELDERBERRY JUICE; POTASSIUM SORBATE; SODIUM BENZOATE; CITRIC ACID MONOHYDRATE

Ology Acne Spot

Active ingredients

Salicylic Acid 1.8%

Purpose

Acne Medication

Uses

- For the treatment of acne blemishes, acne pimples, blackheads, and whiteheads and allows skin to heal.

Warnings

For external use only.

When using this product

skin irritation or dryness may occur, especially if used with other topical acne medication. If it occurs, use only one ance treatment at a time, and reduce usage to every other day.

KEEP OUT OF REACH OF CHILDREN.

If swallowed, get medical help or contact a Poison Control Center immediately.

Directions

- Clean the skin thoroughly before applying this product.
- Cover the entire affected area with a thin layer one to three times daily.
- Because excessive drying of the skin may occur, start with one application daily, then gradually increase to two or three times daily if needed or as directed by a doctor.
- If bothersome dryness or peeling occurs, reduce application to once a day or every other day.

Other information

- Avoid storing at extreme temperatures (Below 40ºF and above 100ºF).

Inactive ingredients

Aqua (Water), 1,3 Propanediol, Glycerin, Azelaic Acid, Caprylyl Glycol, Aloe Barbadensis Leaf Juice, Polyacrylate Crosspolymer-6, Gaultheria Procumbens (Wintergreen) Leaf Extract, Ethylhexylglycerin, Sodium Hydroxide, Dipotassium Glycyrrhizate, Spiraea Ulmaria Flower Extract, Zinc PCA, Salix Alba (willow) Bark Extract, Sambucus Nigra Fruit Juice, 2-Methlpropan-2-ol, Potassium Sorbate, Sodium Benzoate, Citric Acid